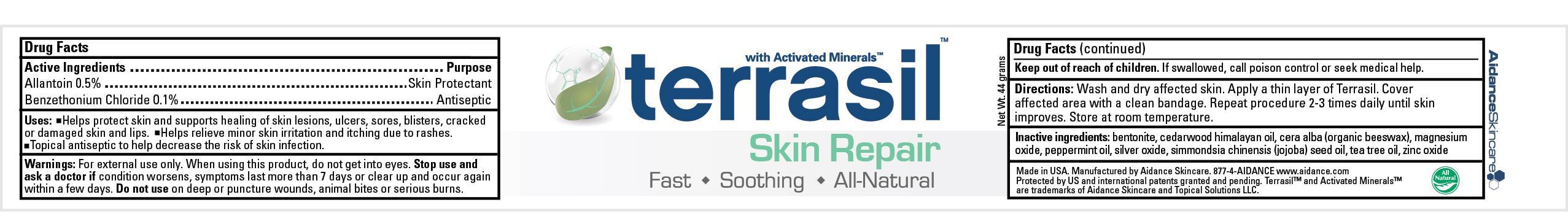 DRUG LABEL: Terrasil Skin Repair
NDC: 24909-131 | Form: OINTMENT
Manufacturer: Aidance Skincare & Topical Solutions, LLC
Category: otc | Type: HUMAN OTC DRUG LABEL
Date: 20120905

ACTIVE INGREDIENTS: ALLANTOIN 0.5 g/100 g; BENZETHONIUM CHLORIDE 0.1 g/100 g
INACTIVE INGREDIENTS: BENTONITE; CEDRUS DEODARA WOOD OIL; JOJOBA OIL; MAGNESIUM OXIDE; PEPPERMINT OIL; SILVER OXIDE; TEA TREE OIL; WHITE WAX; ZINC OXIDE

Drug Facts

Active Ingredients

Allantoin 0.5%

Benzethonium Chloride 0.1%

Purpose

Allantoin - Skin Protectant

Benzethonium Chloride - Antiseptic

Uses

- Helps protect skin and supports healing of skin lesions, ulcers, sores, blisters, cracked or damaged skin and lips.
- Helps relieve minor skin irritation and itching due to rashes.
- Topical antiseptic to help decrease the risk of skin infection.

Warnings

For external use only.

When using this product

Do not get into eyes.

Stop use and ask a doctor if

Condition worsens, symptoms last more than 7 days or clear up and occur again within a few days.

Do not use

On deep or puncture wounds, animal bites or serious burns.

Keep out of reach of children.

If swallowed, call poison control or seek medical help.

Directions

Wash and dry affected skin. Apply a thin layer of Terrasil. Cover affected area with a clean bandage. Repeat procedure 2-3 times daily until skin improves. Store at room temperature.

Inactive Ingredients

bentonite, cedarwood himalayan oil, cera alba (organic beeswax), magnesium oxide, peppermint oil, silver oxide, simmondsia chinensis (jojoba) seed oil, tea tree oil, zinc oxide